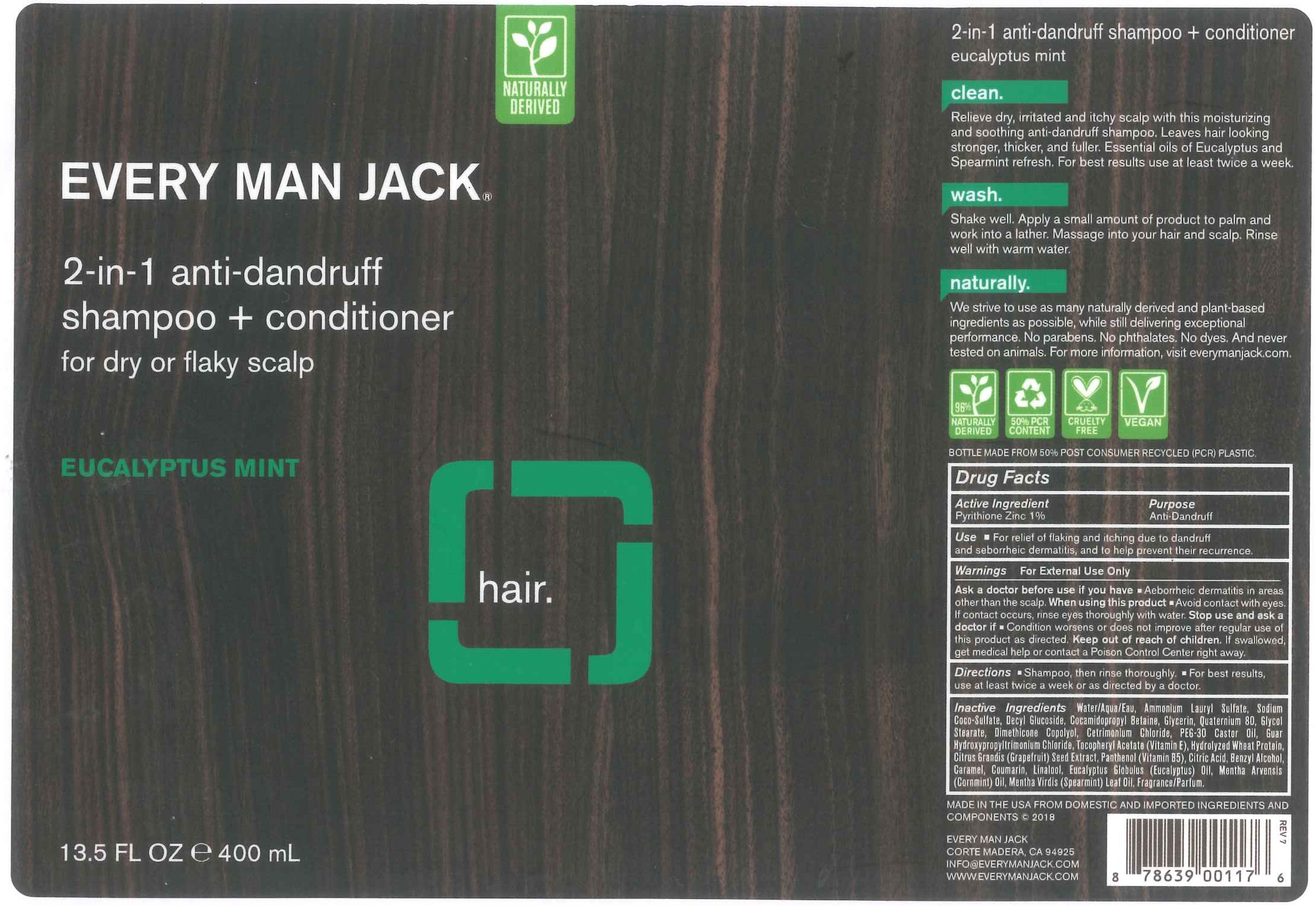 DRUG LABEL: EVERY MAN JACK 2-IN-1 ANTI-DANDRUFF
NDC: 57934-5011 | Form: SHAMPOO
Manufacturer: EVERY MAN JACK
Category: otc | Type: HUMAN OTC DRUG LABEL
Date: 20211217

ACTIVE INGREDIENTS: PYRITHIONE ZINC 1 g/100 mL
INACTIVE INGREDIENTS: CITRUS MAXIMA SEED; PANTHENOL; ANHYDROUS CITRIC ACID; BENZYL ALCOHOL; CARAMEL; COUMARIN; LINALOOL, (+)-; EUCALYPTUS GLOBULUS LEAF; MENTHA ARVENSIS LEAF OIL; SPEARMINT OIL; WATER; AMMONIUM LAURYL SULFATE; SODIUM COCO-SULFATE; DECYL GLUCOSIDE; COCAMIDOPROPYL BETAINE; GLYCERIN; QUATERNIUM-82; GLYCOL STEARATE; PEG/PPG-18/18 DIMETHICONE; CETRIMONIUM CHLORIDE; PEG-30 CASTOR OIL; GUAR HYDROXYPROPYLTRIMONIUM CHLORIDE (1.7 SUBSTITUENTS PER SACCHARIDE); .ALPHA.-TOCOPHEROL ACETATE; HYDROLYZED WHEAT PROTEIN (ENZYMATIC, 3000 MW)

EVERY MAN JACK 2-IN-1 ANTI-DANDRUFF - 57934-5011

ACTIVE INGREDIENT

PYRITHIONE ZINC 1%

PURPOSE

ANTI DANDRUFF

USE

- FOR RELIEF OF FLAKING AND ITCHING DUE TO DANDRUFF AND SEBORRHEIC DERMATITIS , AND TO HELP PREVENT THEIR RECURRENCE.

WARNINGS

FOR EXTERNAL USE ONLY.ASK A DOCTOR BEFORE USE IF YOU HAVE

- ABORRHEIC DERMATITIS IN AREAS OTHER THAN SCALP.

WHEN USING THIS PRODUCT

- AVOID CONTACT WITH EYES. IF CONTACT OCCURS, RINSE EYES THOROUGHLY WITH WATER.

STOP USE AND ASK A DOCTOR IF

- CONDITION WORSENS OR DOES NOT IMPROVE AFTER REGULAR USE OF THIS PRODUCT AS DIRECTED.

KEEP OUT OF REACH OF CHILDREN

KEEP OUT OF REACH OF CHILDRN. IF SWALLOWED, GET MEDICAL HELP OR CONTACT A POISON CONTROL CENTER RIGHT AWAY.

DIRECTIONS

- SHAMPOO, THEN RINSE THOROUGHLY.
- FOR BEST RESULTS, USE AT LEAST TWICE A WEEK OR ASDIRECTED BY A DOCTOR.

INACTIVE INGREDIENTS

WATER/AQUA/EAU, AMMONIUM LAURYL SULFATE, SODIUM COCO-SULFATE, DECYL GLUCOSIDE, COCAMIDOPROPYL BETAINE, GLYCERIN, QUATERNIUM 80, GLYCOL STEARATE, DIMETHICONE COPOLYOL, CETRIMONIUM CHLORIDE, PEG-30 CASTOR OIL, GUAR HYDROXYPROPYLTRIMONIUM CHLORIDE, TOCOPHERYL ACETATE (VITAMIN E), HYDROLYZED WHEAT PROTEIN,CITRUS GRANDIS (GRAPEFRUIT) SEED EXTRACT, PANTHENOL (VITAMIN B5), CITRIC ACID, BENZYL ALCOHOL, CARAMEL, COUMARIN, LINALOOL, EUCALYPTUS GLOBULUS (EUCALYPTUS) OIL, MENTHA ARVENSIS (CORNMINT) OIL, MENTHA VIRDIS (SPEARMINT) LEAF OIL, FRAGRANCE/PARFUM.